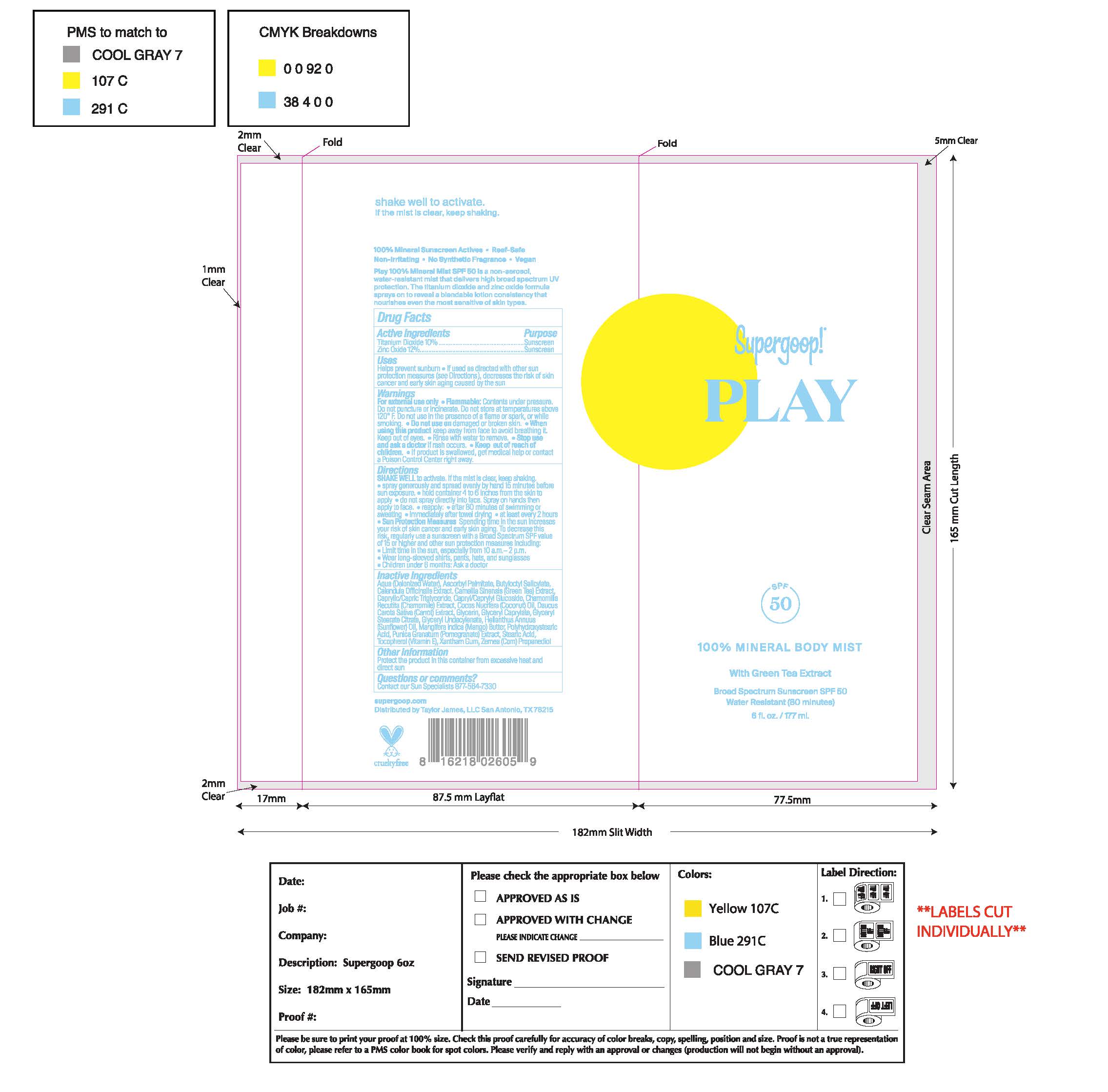 DRUG LABEL: 100% Mineral Body Mist With Green Tea Extract Broad Spectrum SPF 50
NDC: 75936-212 | Form: LIQUID
Manufacturer: Supergoop, LLC
Category: otc | Type: HUMAN OTC DRUG LABEL
Date: 20221011

ACTIVE INGREDIENTS: TITANIUM DIOXIDE 10 g/100 mL; ZINC OXIDE 12 g/100 mL
INACTIVE INGREDIENTS: CAPRYLYL GLUCOSIDE; POLYHYDROXYSTEARIC ACID (2300 MW); GLYCERYL CAPRYLATE; PUNICA GRANATUM ROOT BARK; COCONUT OIL; CARROT; GREEN TEA LEAF; GLYCERIN; GLYCERYL STEARATE CITRATE; ASCORBYL PALMITATE; SUNFLOWER OIL; XANTHAN GUM; WATER; GLYCERYL 1-UNDECYLENATE; CALENDULA OFFICINALIS FLOWER; MEDIUM-CHAIN TRIGLYCERIDES; BUTYLOCTYL SALICYLATE; MATRICARIA CHAMOMILLA WHOLE; STEARIC ACID; TOCOPHEROL; MANGIFERA INDICA SEED BUTTER; PROPANEDIOL

100% Mineral Body Mist With Green Tea Extract Broad Spectrum SPF 50

Active Ingredients Purpose

Titanium Dioxide 10% Sunscreen

Zinc Oxide 12% Sunscreen

Uses

Helps Prevent Sunburn
If used as directed with other sun protection measures (see Directions), decreases the risk of skin cancer and early skin aging caused by the sun.

Keep out of reach of children. If product is swallowed, get medical help or contact a poison Control Center right away

Stop use and ask a doctor if rash occurs

WARNINGS

For external use only

Flammable: Contents under pressure. Do not puncture or incinerate. Do not store at temperatures above 120F. Do not use in the presence of a flame or spark or while smoking.

Do not use on damaged or broken skin

When using this product, keep away from face to avoid breathing it. Keep out of eyes

Rinse with water to remove.

Directions

SHAKE WELL to activate, if the mist is clear, keep shaking.

- spray generously and spread evenly by hand 15 minutes before sun exposure
- hold container 4 to 6 inches from the skin to apply
- do not spray directly into face. Spray on hands then apply to face
- reapply:
- After 80 minutes of swimming or sweating
- Immediately after towel drying
- At least every 2 hours.
- Sun Protection Measures Spending time in the sun increases your risk of skin cancer and early skin aging. To decrease this risk, regularly use a sunscreen with a Broad-Spectrum SPF value of 15 or higher and other sun protection measures including:

• limit your time in the sun, especially from 10 a.m. – 2 p.m.

• wear long-sleeved shirts, pants, hats, and sunglasses

• Children under 6 months of age: ask a doctor.

Inactive ingredients

Aqua (Deionized Water), Ascorbyl Palmitate, Butyloctyl Salicylate, Calendula Officinalis Extract, Camellia Sinensis (Green Tea) Extract, Caprylic/Capric Triglyceride, Capryl/Caprylyl Glucoside, Chamomilla Recutita (Chamomile) Extract, Cocos Nucifera (Coconut) Oil, Daucus Carota Sativa (Carrot) Extract, Glycerin, Glyceryl Caprylate, Glyceryl Stearate Citrate, Glyceryl Undecylenate, Helianthus Annuus (Sunflower) Oil, Mangifera Indica (Mango) Butter, Polyhydroxystearic Acid, Punica Granatum (Pomegranate) Extract, Stearic Acid, Tocopherol (Vitamin E), Xanthan Gum, Zemea (Corn) Propanediol

PACKAGE LABEL

Supergoop!

PLAY

SPF 50

100% Mineral Body Mist

With Green Tea Extract

Broad Spectrum Sunscreen SPF 50

Water Resistant (80 minutes)

6 fl. oz. / 177 ml.